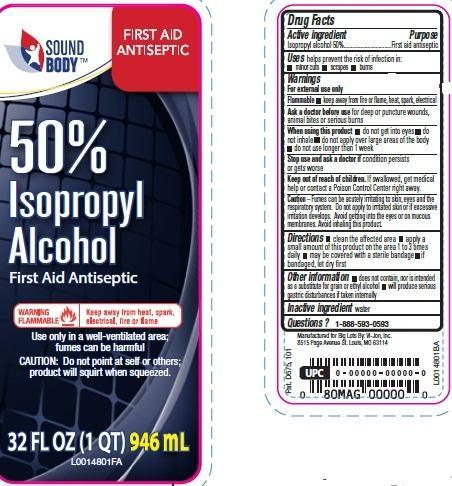 DRUG LABEL: 50% Rubbing
NDC: 11344-003 | Form: LIQUID
Manufacturer: Sound Body
Category: otc | Type: HUMAN OTC DRUG LABEL
Date: 20210519

ACTIVE INGREDIENTS: ISOPROPYL ALCOHOL 500 mg/1 mL
INACTIVE INGREDIENTS: WATER

Sound Body 864.003 864AC

Active ingredient

Isopropyl alcohol 50%

Purpose

First aid antiseptic

Use

helps prevent the risk of infection in:

- minor cuts
- scarapes
- burns

Warnings

For external use only

Flammable

keep away from fire or flame, heat spark, electrical

Ask a doctor before use

If you have deep or puncture wounds, animal bites or serious burns

When using this product

- do not get into eyes
- do not inhale
- do not apply over large areas of the body
- do not use longer than 1 week

Stop use and ask a doctor

if condition persists or gets worse

keep out of children

If swallowed, get medical help or contact a Poison Control Center right away.

Caution

Fumes can be acutely irritating to skin, eyes and the respiratory system. Do not apply to irritated skin or if excessive irritation develops. Avoid getting into eyes or on mucous membranes. Avoid inhaling this product.

Directions

- clean the affected area
- apply a small amount of the is product on the affected area 1 to 3 times daily
- may be covered with a sterile bandage
- if bandaged, let dry first

Other Information

- does not contain, nor is intended as a substitute for grain or ethyl alcohol
- will produce serious gastric distrubances if taken internally

Inactive ingredient

water

Adverse reactions

Manufactured for Big Lots By: Vi-Jon, LLC

8515 Page Avenue St. Louis, MO 63114

864.003/864AC

principal display panel

SOUND

BODY

FIRST AID

ANTISPETIC

50%

Isopropyl

Alcohol

First Aid Antispetic

WARNING FLAMMABLE - Keep away from heat, spark, electrical, fire or flame

Use only in a well-ventilated area; fumes can be harmful

CAUTION: Do not point at self or others; product will squirt when squeezed.

32 FL OZ (1 QT) 946 mL